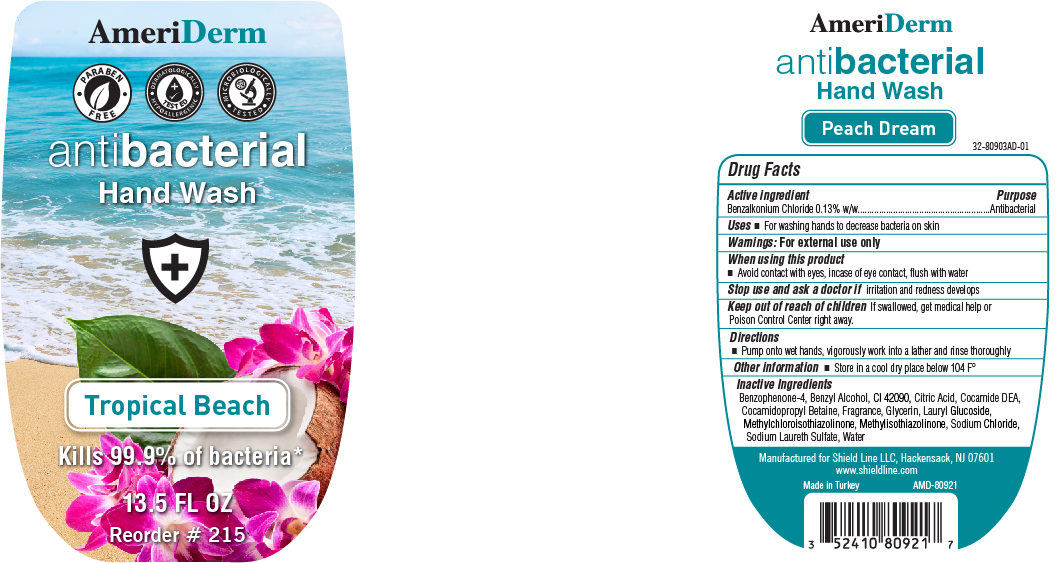 DRUG LABEL: MedPride Antibacterial Hand Wash
NDC: 52410-8092 | Form: LIQUID
Manufacturer: Shield Line LLC
Category: otc | Type: HUMAN OTC DRUG LABEL
Date: 20220113

ACTIVE INGREDIENTS: BENZALKONIUM CHLORIDE 0.13 g/100 g
INACTIVE INGREDIENTS: COCO DIETHANOLAMIDE; CITRIC ACID MONOHYDRATE; SULISOBENZONE; SODIUM CHLORIDE; LAURYL GLUCOSIDE; METHYLCHLOROISOTHIAZOLINONE; GLYCERIN; METHYLISOTHIAZOLINONE; SODIUM LAURETH SULFATE; WATER; COCAMIDOPROPYL BETAINE; FD&C BLUE NO. 1; BENZYL ALCOHOL

Antibacterial Hand Soap- Tropical Beach

Drug Facts

Active Ingredient

Benzalkonium Chloride 0.13%(w/w)

Purpose

Antibacterial

Uses

- For washing hand to decrease bacteria on the skin

Warnings

For external use only

When using this product

- Avoid contact with eyes. In case of eye contact, flush with water.

Stop use and ask a doctor if

irritation and redness develops

Keep out of reach of children

If swallowed, get medical help or contact a Poison Control Center right away.

Directions

pump onto wet hands, vigorously work into lather rinse thoroughly

other information

Store in a cool dry place below 104 F

Inactive Ingredients

Benzophenone-4, Benzyl Alcohol, CI 42090, Citric Acid, Cocamide DEA, Cocamidopropyl Betaine, Fragrance, Glycerin, Lauryl Glucoside, Methylchloroisothiazolinone, Methylisothiazolinone, Sodium Chloride, Sodium Laureth Sulfate, Water